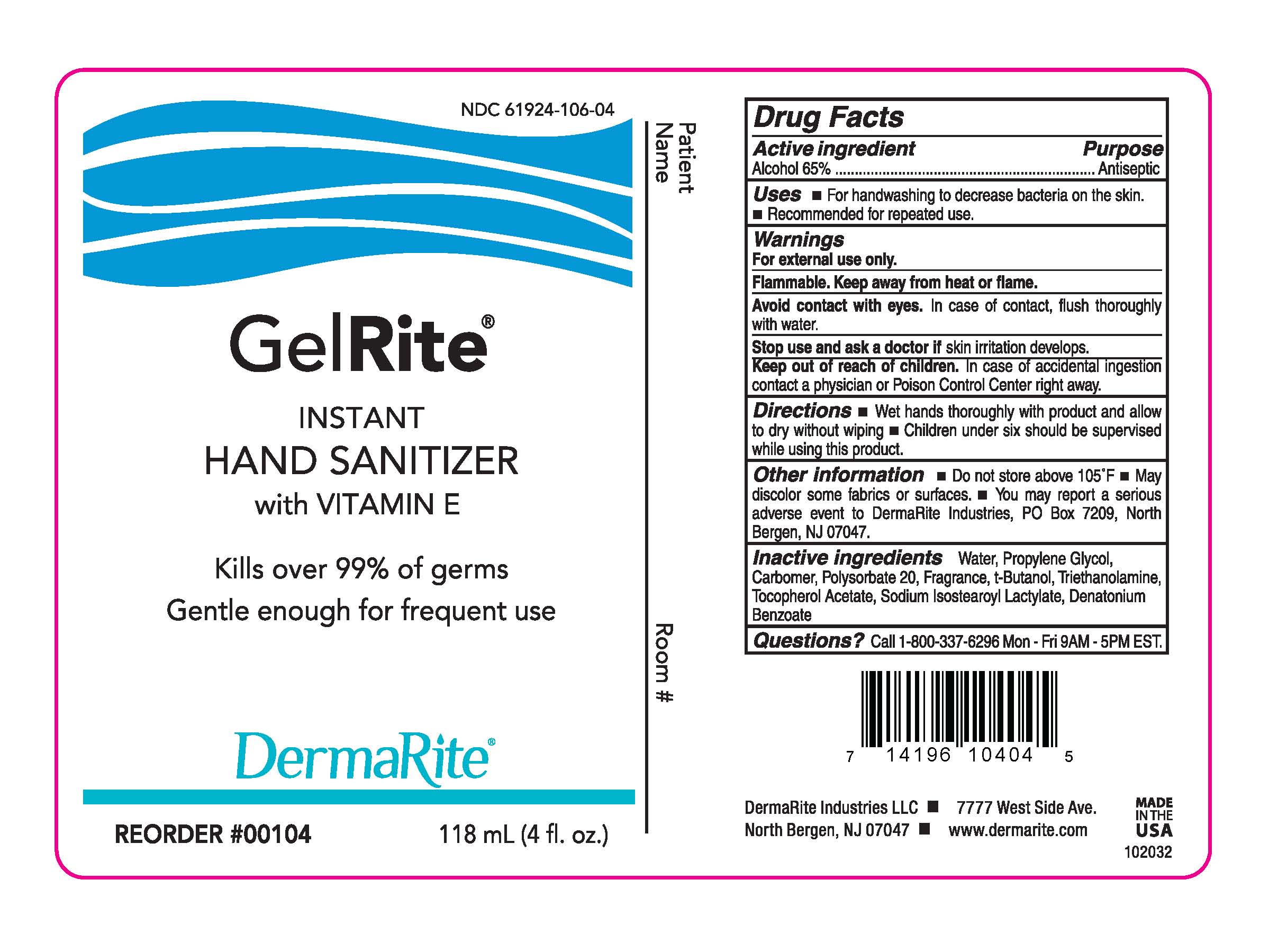 DRUG LABEL: GELRITE
NDC: 61924-106 | Form: GEL
Manufacturer: DERMARITE INDUSTRIES, LLC
Category: otc | Type: HUMAN OTC DRUG LABEL
Date: 20241205

ACTIVE INGREDIENTS: ALCOHOL 65 mL/100 mL
INACTIVE INGREDIENTS: WATER; CARBOMER 940; DENATONIUM BENZOATE ANHYDROUS; .ALPHA.-TOCOPHEROL ACETATE; PROPYLENE GLYCOL 1,2-DISTEARATE; BUTANOL (MIXED ISOMERS); 2,4,5-T-TROLAMINE; SODIUM ISOSTEAROYL LACTYLATE

GELRITE

Active Ingredient

Alcohol 65%

Purpose

Skin Protectant

Uses

- For handwashing to decrease bacteria on skin.
- Recommended for repeated use.

Warnings

For external use only.

Flammable. Keep away from heat and flame.

Avoid contact with eyes. In case of contact, flush thoroughly with water.

Stop use and ask a doctor if skin irritation develops.

.

Directions

- Wet hands thoroughly with product and allow to dry without wiping.
- Children under six should be supervised while using this product.

Other Information

- Do not store above 105°F
- May discolor some fabrics or surfaces
- You may report a serious adverse event to DermaRite Industries, PO Box 7209, North Bergen, NJ 07047

Inactive ingredients

Water, Propylene Glycol, Carbomer, Polysorbate 20, Fragrance, t-Butanol, Triethanolamine, Tocopherol Acetate, Sodium Isostearoyl Lactate, Denatonium Benzoate

Questions?

Call 1-800-337-6296 Mon-Fri 9AM-5PM EST.

Keep out of reach of children. In case of accidental ingestion contact a physician or Poison Control Center right away